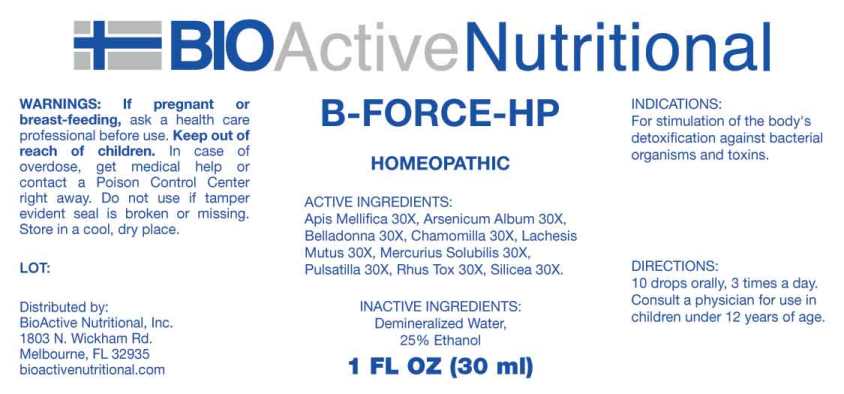 DRUG LABEL: B Force HP
NDC: 43857-0574 | Form: LIQUID
Manufacturer: BioActive Nutritional, Inc.
Category: homeopathic | Type: HUMAN OTC DRUG LABEL
Date: 20230606

ACTIVE INGREDIENTS: APIS MELLIFERA 30 [hp_X]/1 mL; ARSENIC TRIOXIDE 30 [hp_X]/1 mL; ATROPA BELLADONNA 30 [hp_X]/1 mL; MATRICARIA RECUTITA 30 [hp_X]/1 mL; LACHESIS MUTA VENOM 30 [hp_X]/1 mL; MERCURIUS SOLUBILIS 30 [hp_X]/1 mL; PULSATILLA PRATENSIS WHOLE 30 [hp_X]/1 mL; TOXICODENDRON PUBESCENS LEAF 30 [hp_X]/1 mL; SILICON DIOXIDE 30 [hp_X]/1 mL
INACTIVE INGREDIENTS: WATER; ALCOHOL

DRUG FACTS:

ACTIVE INGREDIENTS:

Apis Mellifica 30X, Arsenicum Album 30X, Belladonna 30X, Chamomilla 30X, Lachesis Mutus 30X, Mercurius Solubilis 30X, Pulsatilla (Pratensis) 30X, Rhus Tox 30X, Silicea 30X

INDICATIONS:

For stimulation of the body's detoxification against bacterial organisms and toxins.

WARNINGS:

If pregnant or breast-feeding, ask a health care professional before use.

Keep out of reach of children. In case of overdose, get medical help or contact a Poison Control Center right away.

Do not use if tamper evident seal is broken or missing.

Store in cool, dry place.

Keep out of reach of children. In case of overdose, get medical help or contact a Poison Control Center right away.

DIRECTIONS:

10 drops orally, 3 times a day. Consult a physician for use in children under 12 years of age.

INDICATIONS:

For stimulation of the body's detoxification against bacterial organisms and toxins.

INACTIVE INGREDIENTS:

Demineralized Water, 25% Ethanol.

QUESTIONS:

Distributed by:

BioActive Nutritional, Inc.

1803 N. Wickham Rd.

Melbourne, FL 32935

bioactivenutritional.com

PACKAGE LABEL DISPLAY:

BioActive Nutritional

B-FORCE HP

Homeopathic

1 FL OZ (30 ml)